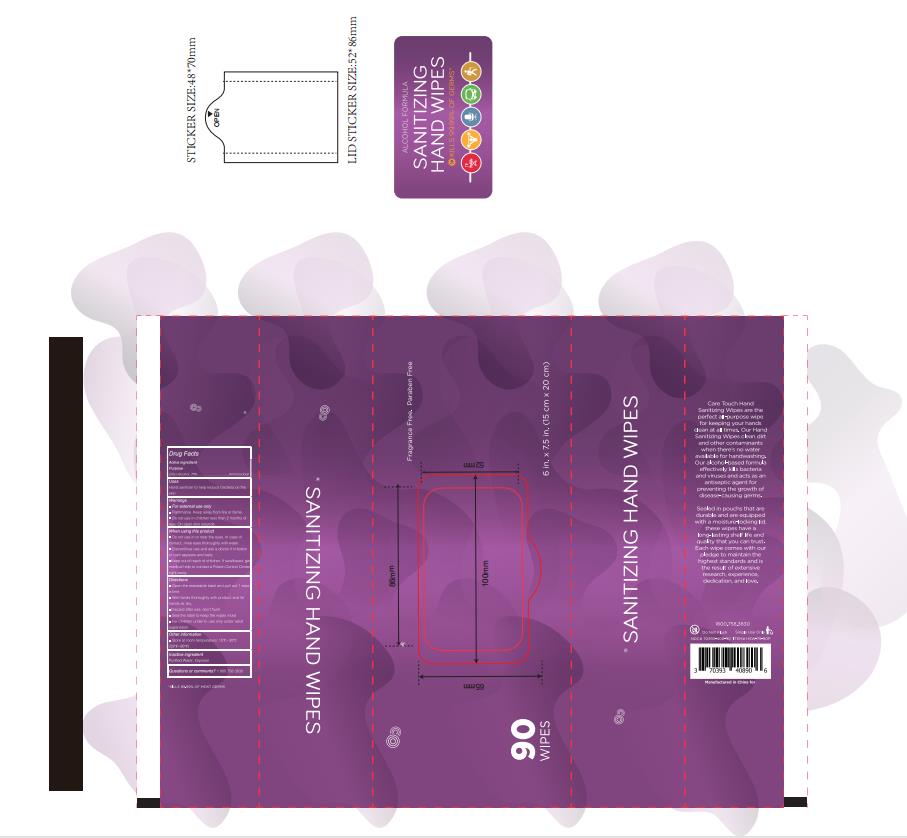 DRUG LABEL: Sanitizing Wipes
NDC: 78936-006 | Form: CLOTH
Manufacturer: Hangzhou Caring Cleaning Commodity Co.,Ltd
Category: otc | Type: HUMAN OTC DRUG LABEL
Date: 20200703

ACTIVE INGREDIENTS: ALCOHOL 75 mg/100 mL
INACTIVE INGREDIENTS: WATER; GLYCERIN

Sanitizing Wipes

Active Ingredient(s)

Ethyl Alcohol 75%

Purpose

Antimicrobial

Use

To help reduce bacteria on skin

Warnings

- For external use only.
- Flammable, keep product away from fire or flame.
- Do not use in children less than 2 months of age
- On open skin wounds

When using this product

- Do not use in or near the eyes. In case of contact,rinse eyes thoroughly with water.
- Discontinue use and ask a doctor if irritation or rash appears and lasts.

Stop use and ask a doctor if irritation or rash occurs. These may be signs of a serious condition.

Keep out of reach of children. If swallowed, get medical help or contact a Poison Control Center right away.

Inactive ingredients

Purified Water,Glycerin

Directions

- Open the resealable label and pull out 1 wipe a time.
- Wet hands thoroughly with product and let hands air dry.
- Discard after use, don't flush.
- Seal the label to keep the wipes moist.
- For children under 6, use only under adult supervision.

Other information

Store at room temperature: 15℃-30℃(59-86F)

Questions or comments?

1 800 758 3830

Package Label - Principal Display Panel

90 POUCH IN 1 BAG NDC: 78936-006-01